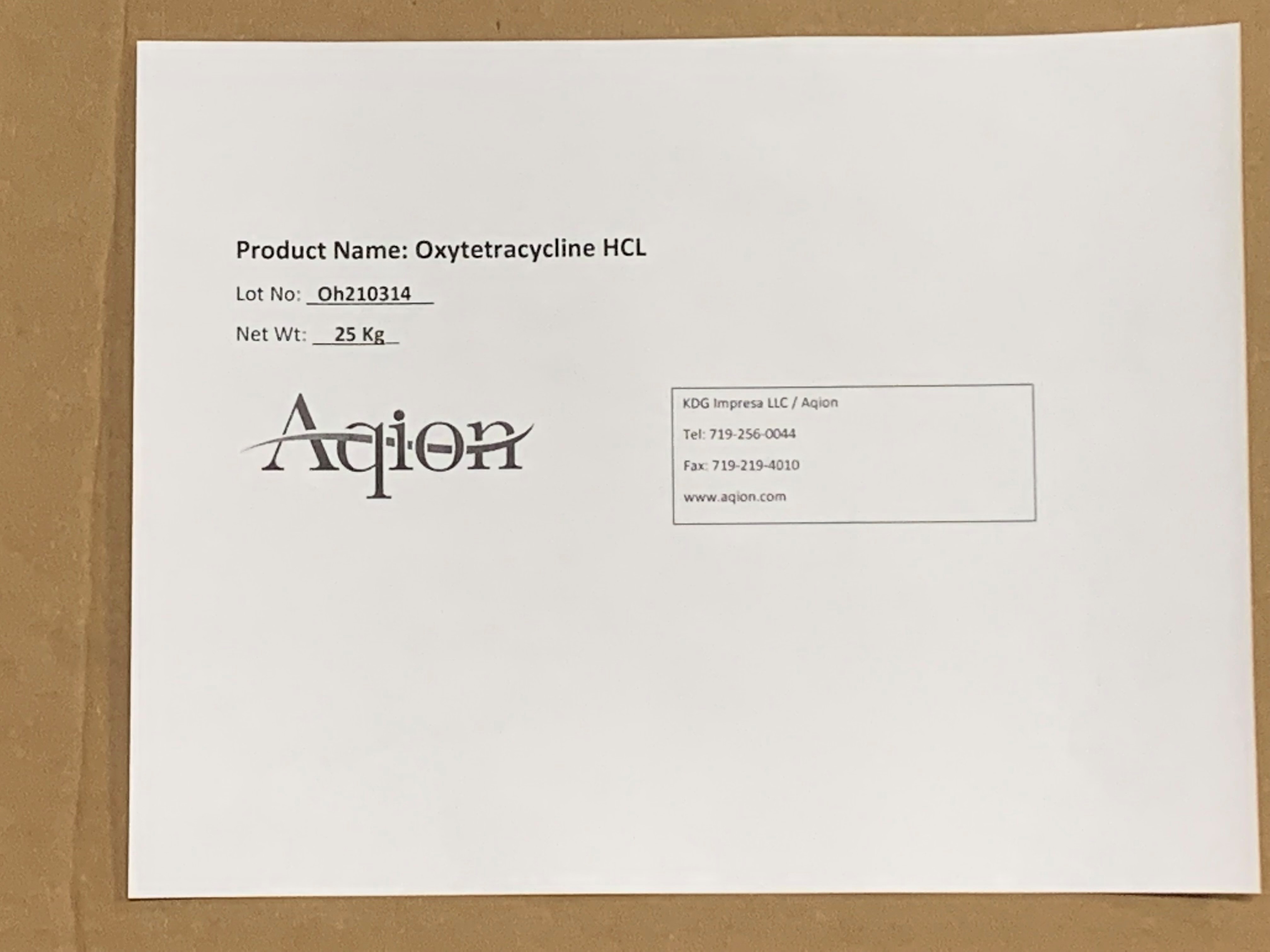 DRUG LABEL: Oxytetracycline HCL
NDC: 43457-528 | Form: POWDER
Manufacturer: KDG Impresa LLC, Aqion
Category: other | Type: BULK INGREDIENT - ANIMAL DRUG
Date: 20220217

ACTIVE INGREDIENTS: OXYTETRACYCLINE HYDROCHLORIDE 1 kg/1 kg

Oxytetracycline HCL